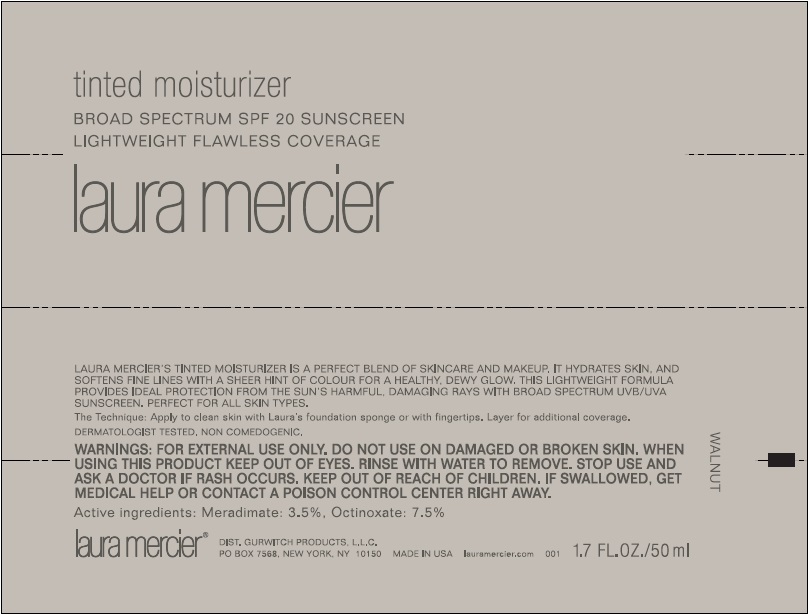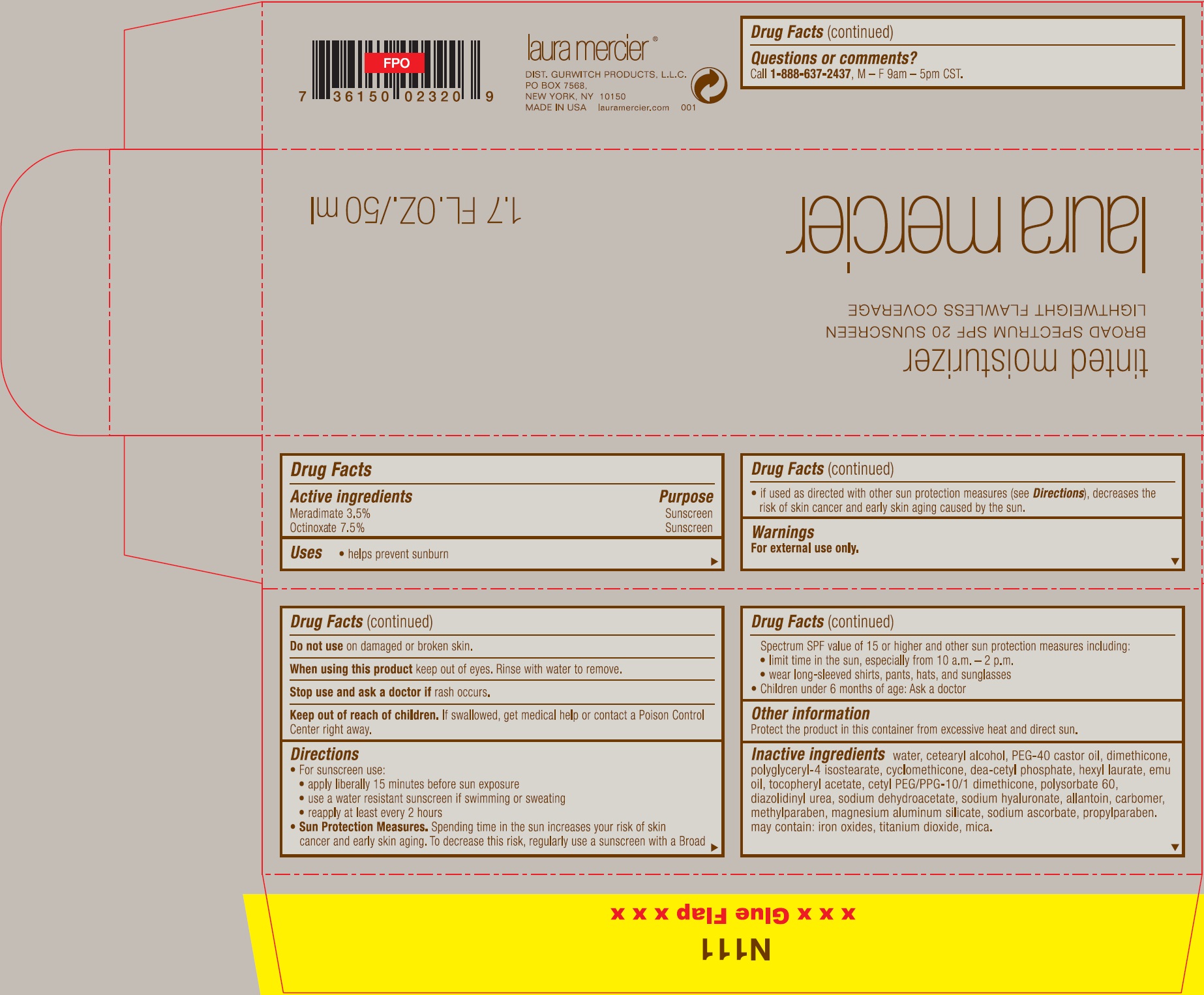 DRUG LABEL: Laura Mercier Tinted Moisturizer Broad Spectrum SPF 20 Sunscreen Walnut
NDC: 65342-7600 | Form: CREAM
Manufacturer: Gurwitch Products, LLC
Category: otc | Type: HUMAN OTC DRUG LABEL
Date: 20170106

ACTIVE INGREDIENTS: MERADIMATE 35 mg/1 mL; OCTINOXATE 75 mg/1 mL
INACTIVE INGREDIENTS: WATER; CETOSTEARYL ALCOHOL; PEG-40 CASTOR OIL; DIMETHICONE; POLYGLYCERYL-4 ISOSTEARATE; CYCLOMETHICONE; DIETHANOLAMINE CETYL PHOSPHATE; HEXYL LAURATE; EMU OIL; .ALPHA.-TOCOPHEROL ACETATE; POLYSORBATE 60; DIAZOLIDINYL UREA; SODIUM DEHYDROACETATE; HYALURONATE SODIUM; ALLANTOIN; CARBOXYPOLYMETHYLENE; METHYLPARABEN; MAGNESIUM ALUMINUM SILICATE; SODIUM ASCORBATE; PROPYLPARABEN

Laura Mercier Tinted Moisturizer Broad Spectrum SPF 20 Sunscreen Walnut

Active ingredients

Meradimate 3.5%
Octinoxate 7.5%

Purpose

Sunscreen

Uses

• helps prevent sunburn
• if used as directed with other sun protection measures (see Directions), decreases the risk of skin cancer and early skin aging caused by the sun.

Warnings

For external use only.

Do not use

on damaged or broken skin.

When using this product

keep out of eyes. Rinse with water to remove.

Stop use and ask a doctor if

rash occurs.

Keep out of reach of children.

If swallowed, get medical help or contact a Poison Control Center right away.

Directions

• For sunscreen use:
• apply liberally 15 minutes before sun exposure
• use a water resistant sunscreen if swimming or sweating
• reapply at least every 2 hours
• Sun Protection Measures. Spending time in the sun increases your risk of skin cancer and early skin aging. To decrease this risk, regularly use a sunscreen with a Broad Spectrum SPF value of 15 or higher and other sun protection measures including:
• limit time in the sun, especially from 10 a.m. – 2 p.m.
• wear long-sleeved shirts, pants, hats, and sunglasses
• Children under 6 months of age: Ask a doctor

Other information

Protect the product in this container from excessive heat and direct sun.

Inactive Ingredients

water, cetearyl alcohol, PEG-40 castor oil, dimethicone, polyglyceryl-4 isostearate, cyclomethicone, dea-cetyl phosphate, hexyl laurate, emu oil, tocopheryl acetate, cetyl PEG/PPG-10/1 dimethcone, polysorbate 60, diazolidinyl urea, sodium dehydroacetate, sodium hyaluronate, allantoin, carbomer, methylparaben, magnesium aluminum silicate, sodium ascorbate, propylparaben. may contain: iron oxides, titanium dioxide, mica.

Questions or comments?

Call 1-888-637-2437, M - F 9am - 5pm CST.